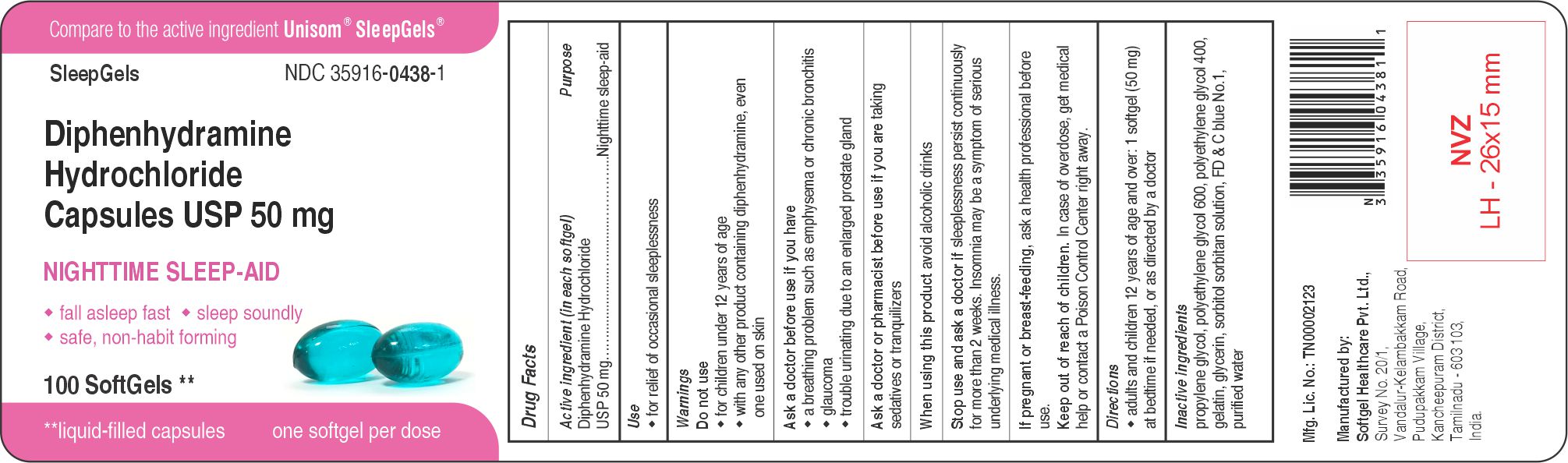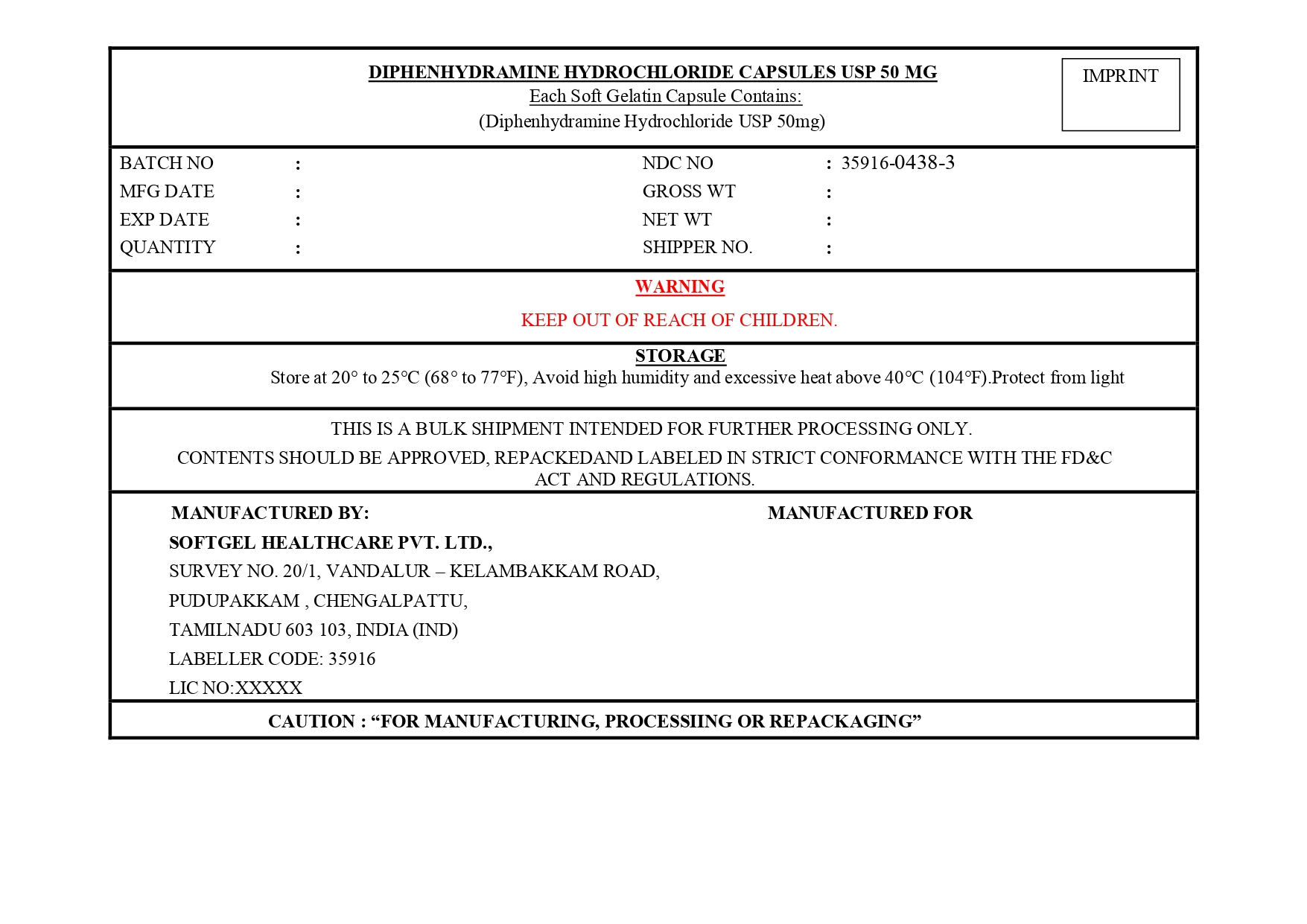 DRUG LABEL: DIPHENHYDRAMINE HYDROCHLORIDE
NDC: 35916-0438 | Form: CAPSULE, LIQUID FILLED
Manufacturer: SOFTGEL HEALTHCARE PRIVATE LIMITED
Category: otc | Type: HUMAN OTC DRUG LABEL
Date: 20260127

ACTIVE INGREDIENTS: DIPHENHYDRAMINE HYDROCHLORIDE 50 mg/1 1
INACTIVE INGREDIENTS: POLYETHYLENE GLYCOL 600; WATER; PROPYLENE GLYCOL; POLYETHYLENE GLYCOL 400; SORBITOL; FD&C BLUE NO. 1; GELATIN; GLYCERIN

Diphenhydramine Hydrochloride Capsules USP 50 mg

Active ingredient

(in each softgel)

Diphenhydramine Hydrochloride USP 50 mg

Purpose

Nighttime sleep-aid

Uses

- for relief of occasional sleeplessness

Warnings

Do not use

- for children under 12 years of age
- with any other product containing diphenhydramine, even one used on skin

Ask a doctor before use if you have

- a breathing problem such as emphysema or chronic bronchitis
- glaucoma
- trouble urinating due to an enlarged prostate gland

Ask a doctor or pharmacist before use if you are

taking sedatives or tranquilizers

When using this product

avoid alcoholic drinks

Stop use and ask a doctor if

sleeplessness persist continuously for more than 2 weeks. Insomnia may be a symptom of a serious underlying medical illness.

If pregnant or breast-feeding,

ask a health professional before use.

Keep out of reach of children.

In case of overdose, get medical help or contact a Poison Control Center right away.

Directions

- adults and children 12 years of age and over: 1 softgel (50 mg) at bedtime if needed, or as directed by a doctor

Inactive ingredients

Propylene Glycol, Polyethylene Glycol 600, Polyethylene Glycol 400, Gelatin, Glycerin, Sorbitol Sorbitan Solution, FD & C Blue No.1, Purified Water

Principal Display Panel

Compare to the active ingredient Unisom® SleepGels®

SleepGels

NDC 35916-0438-1

Diphenhydramine Hydrochloride Capsules USP 50 mg

NIGHTTIME SLEEP-AID

♦ fall asleep fast ♦ sleep soundly

♦ safe, non-habit forming

100 SoftGels**

**liquid-filled capsules

one softgel per dose